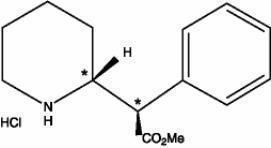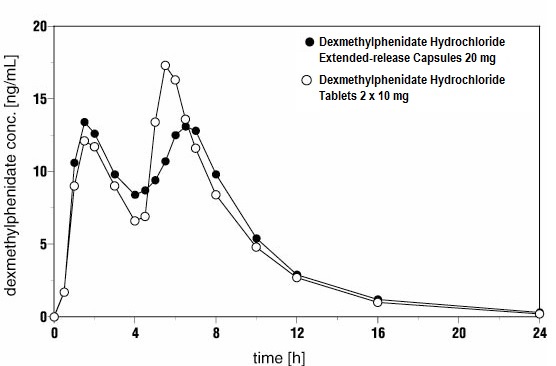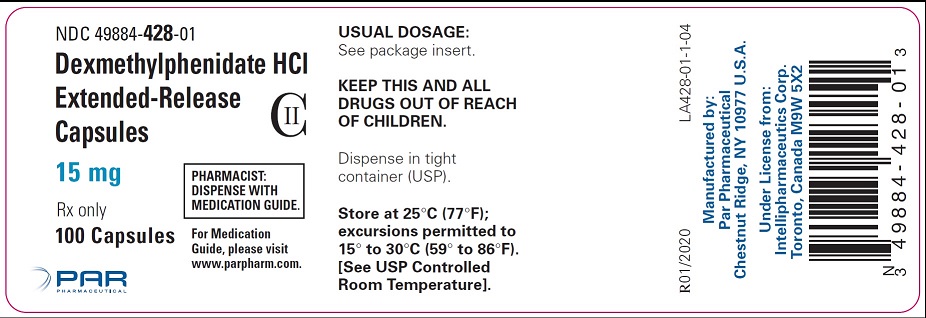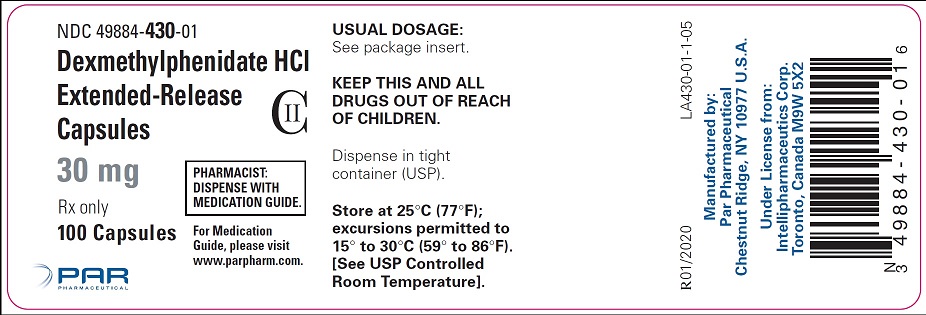 DRUG LABEL: Dexmethylphenidate Hydrochloride


NDC: 49884-428 | Form: CAPSULE, EXTENDED RELEASE
Manufacturer: Par Health USA, LLC
Category: prescription | Type: HUMAN PRESCRIPTION DRUG LABEL
Date: 20260105
DEA Schedule: CII

ACTIVE INGREDIENTS: DEXMETHYLPHENIDATE HYDROCHLORIDE 15 mg/1 1
INACTIVE INGREDIENTS: SUCROSE; METHACRYLIC ACID; TRIETHYL CITRATE; TALC; SILICON DIOXIDE; HYPROMELLOSE, UNSPECIFIED; POLYDEXTROSE; TRIACETIN; POLYETHYLENE GLYCOL, UNSPECIFIED; FD&C YELLOW NO. 6; FD&C BLUE NO. 2; TITANIUM DIOXIDE; GELATIN

HIGHLIGHTS OF PRESCRIBING INFORMATION

These highlights do not include all the information needed to use DEXMETHYLPHENIDATE HYDROCHLORIDE EXTENDED-RELEASE CAPSULES safely and effectively. See full prescribing information for DEXMETHYLPHENIDATE HYDROCHLORIDE EXTENDED-RELEASE CAPSULES.
DEXMETHYLPHENIDATE HYDROCHLORIDE extended-release capsules, for oral use, CII
Initial U.S. Approval: 2005

WARNING: ABUSE AND DEPENDENCE

See full prescribing information for complete boxed warning

- CNS stimulants, including Dexmethylphenidate Hydrochloride Extended-release Capsules, other methylphenidate-containing products, and amphetamines, have a high potential for abuse and dependence (5.1, 9.2, 9.3).
- Assess the risk of abuse prior to prescribing and monitor for signs of abuse and dependence while on therapy (5.1, 9.2).

1 INDICATIONS AND USAGE

Dexmethylphenidate Hydrochloride Extended-release Capsules is a central nervous system (CNS) stimulant indicated for the treatment of Attention Deficit Hyperactivity Disorder (ADHD) in patients aged 6 years and older

2 DOSAGE AND ADMINISTRATION

- Patients new to methylphenidate: Recommended starting dose is 5 mg once daily for pediatric patients and 10 mg once daily for adults with or without food in the morning (2.2).
- Patients currently on methylphenidate: Dexmethylphenidate Hydrochloride Extended-release Capsules dosage is half the current total daily dosage of methylphenidate (2.2).
- Patients currently on dexmethylphenidate immediate-release tablets: Give the same daily dose of Dexmethylphenidate Hydrochloride Extended-release Capsules (2.2)
- Titrate weekly in increments of 5 mg in pediatric patients and 10 mg in adult patients (2.2).
- Maximum recommended daily dose: 30 mg in pediatric patients and 40 mg in adults (2.2).
- Capsules may be swallowed whole or opened and the entire contents sprinkled on applesauce (2.3).

3 DOSAGE FORMS AND STRENGTHS

Extended-release capsules: 15mg and 30mg of dexmethylphenidate hydrochloride

4 CONTRAINDICATIONS

- Known hypersensitivity to methylphenidate or other components of Dexmethylphenidate Hydrochloride Extended-release Capsules (4)
- Concurrent treatment with a monoamine oxidase inhibitor (MAOI), or use of an MAOI within the preceding 14 days (4)

5 WARNINGS AND PRECAUTIONS

- Serious Cardiovascular Events:Sudden death has been reported in association with CNS stimulant treatment at usual doses in pediatric patients with structural cardiac abnormalities or other serious heart problems. In adults, sudden death, stroke, and myocardial infarction have been reported Avoid use in patients with known structural cardiac abnormalities, cardiomyopathy, serious heart rhythm arrhythmias, or coronary artery disease (5.2).
- Blood Pressure and Heart Rate Increases:Monitor blood pressure and pulse. Consider the benefits and risk in patients for whom an increase in blood pressure or heart rate would be problematic (5.3).
- Psychiatric Adverse Reactions:Use of stimulants may cause psychotic or manic symptoms in patients with no prior history, or exacerbation of symptoms in patients with preexisting psychiatric illness. Evaluate for existing psychotic or bipolar disorder prior to Dexmethylphenidate Hydrochloride Extended-release Capsules use (5.4).
- Priapism:Cases of painful and prolonged penile erections and priapism have been reported with methylphenidate products. Immediate medical attention should be sought if signs or symptoms of prolonged penile erections or priapism are observed (5.5).
- Peripheral Vasculopathy, Including Raynaud’s Phenomenon:Stimulants used to treat ADHD are associated with peripheral vasculopathy, including Raynaud’s phenomenon. Careful observation for digital changes is necessary during treatment with ADHD stimulants (5.6).
- Long-Term Suppression of Growth:Monitor height and weight at appropriate intervals in pediatric patients (5.7).

6 ADVERSE REACTIONS

The most common adverse reactions (greater than or equal to 5% and twice the rate of placebo):

- Pediatric patients 6 to 17 years: dyspepsia, decreased appetite, headache, and anxiety (6.1).
- Adults: dry mouth, dyspepsia, headache, pharyngolaryngeal pain, and anxiety (6.1).

To report SUSPECTED ADVERSE REACTIONS, contact Par Pharmaceutical at 1-800-828-9393 or FDA at 1-800-FDA-1088 orwww.fda.gov/medwatch.

7 DRUG INTERACTIONS

- Antihypertensive Drugs: Monitor blood pressure. Adjust dosage of antihypertensive drug as needed (7.1).
- Halogenated Anesthetics: Avoid use of Dexmethylphenidate Hydrochloride Extended-release Capsules on the day of surgery if halogenated anesthetics will be used (7.1).

FULL PRESCRIBING INFORMATION

WARNING: ABUSE AND DEPENDENCE

CNS stimulants, including Dexmethylphenidate Hydrochloride Extended-release Capsules, other methylphenidate-containing products, and amphetamines, have a high potential for abuse and dependence. Assess the risk of abuse prior to prescribing, and monitor for signs of abuse and dependence while on therapy [see Warning and Precautions (5.1), Drug Abuse and Dependence (9.2, 9.3)] .

1 INDICATIONS AND USAGE

Dexmethylphenidate Hydrochloride Extended-release Capsules is indicated for the treatment of Attention Deficit Hyperactivity Disorder (ADHD) [see Clinical Studies (14)] .

2 DOSAGE AND ADMINISTRATION

Dexmethylphenidate Hydrochloride Extended-release Capsules is for oral administration once daily in the morning.
Dexmethylphenidate Hydrochloride Extended-release Capsules may be swallowed as whole capsules or alternatively may be administered by sprinkling the capsule contents on a small amount of applesauce (see specific instructions below). Dexmethylphenidate Hydrochloride Extended-release Capsules and/or their contents should not be crushed, chewed, or divided.
The capsules may be carefully opened and the beads sprinkled over a spoonful of applesauce. The mixture of drug and applesauce should be consumed immediately in its entirety. The drug and applesauce mixture should not be stored for future use.

Dosage should be individualized according to the needs and responses of the patient.

2.1 Pretreatment Screening

Prior to treating pediatric patients and adults with central nervous system (CNS) stimulants including Dexmethylphenidate Hydrochloride Extended-release Capsules, assess for the presence of cardiac disease (i.e., perform a careful history including family history of sudden death or ventricular arrhythmia, and physical examination) [see Warnings and Precautions (5.2)] .
Assess the risk of abuse prior to prescribing, and monitor for signs of abuse and dependence while on therapy. Maintain
careful prescription records, educate patients about abuse, monitor for signs of abuse and overdose, and periodically
re-evaluate the need for Dexmethylphenidate Hydrochloride Extended-release Capsules use [see Boxed Warning, Warnings and Precautions (5.1), Drug Abuse and Dependence (9)] .

2.2 Treatment of ADHD

Patients New to Methylphenidate
The recommended starting dosage of Dexmethylphenidate Hydrochloride Extended-release Capsules for patients who are not currently taking dexmethylphenidate or racemic methylphenidate, or for patients who are on stimulants other than methylphenidate are:

- Pediatric patients: Start with 5 mg orally once daily in the morning with or without food.

- Adult patients: Start with 10 mg orally once daily in the morning with or without food.

Patients Currently on Methylphenidate
The recommended starting dose of Dexmethylphenidate Hydrochloride Extended-release Capsules for patients currently using methylphenidate is half the total daily dose of racemic methylphenidate.
Patients currently using dexmethylphenidate immediate-release tablets may be given the same daily dose of Dexmethylphenidate Hydrochloride Extended-release Capsules.
Titration Schedule
The dose may be titrated weekly in increments of 5 mg in pediatric patients and 10 mg in adult patients. The dose should be individualized according to the needs and response of the patient. Daily doses above 30 mg in pediatrics and 40 mg in adults have not been studied and are not recommended.
Maintenance/Extended Treatment
Pharmacological treatment of ADHD may be needed for extended periods. Periodically reevaluate the long-term use of Dexmethylphenidate Hydrochloride Extended-release Capsules and adjust dosage as needed.

2.3 Administration Instructions

Dexmethylphenidate Hydrochloride Extended-release Capsules is administered orally and may be taken whole or the capsule may be opened and the entire contents sprinkled onto applesauce. If the patient is using the sprinkled administration method, the sprinkled applesauce should be consumed immediately; it should not be stored. Patients should take the applesauce with sprinkled beads in its entirety without chewing. The dose of a single capsule should not be divided. The contents of the entire capsule should be taken, and patients should not take anything less than one capsule per day.

2.4 Dose Reduction and Discontinuation

If paradoxical aggravation of symptoms or other adverse reactions occur, reduce the dosage, or if necessary, discontinue Dexmethylphenidate Hydrochloride Extended-release Capsules. If improvement is not observed after appropriate dosage adjustment over a one-month period, the drug should be discontinued.

3 DOSAGE FORMS AND STRENGTHS

15 mg extended-release capsules – white opaque cap and body, imprinted in black ink “par” on cap and “428” on body.
30 mg extended-release capsules – white opaque cap and body, imprinted in green ink “par” on cap and “430” on body.

4 CONTRAINDICATIONS

- Hypersensitivity to methylphenidate or other components of Dexmethylphenidate Hydrochloride Extended-release Capsules. Hypersensitivity reactions such as angioedema and anaphylactic reactions have been reported in patients treated with methylphenidate [see Adverse Reactions (6.1)] .
- Concomitant treatment with monoamine oxidase inhibitors (MAOIs) or within 14 days following discontinuation of treatment with an MAOI, because of the risk of hypertensive crises [see Drug Interactions (7.1)] .

5 WARNINGS AND PRECAUTIONS

5.1 Potential for Abuse and Dependence

CNS stimulants, including Dexmethylphenidate Hydrochloride Extended-release Capsules, other methylphenidate-containing products, and amphetamines, have a high potential for abuse and dependence. Assess the risk of abuse prior to prescribing, and monitor for signs of abuse and dependence while on therapy [see Boxed Warning, Drug Abuse and Dependence(9.2, 9.3)] .

5.2 Serious Cardiovascular Reactions

Sudden death, stroke and myocardial infarction have been reported in adults with CNS stimulant treatment at recommended doses. Sudden death has been reported in pediatric patients with structural cardiac abnormalities and other serious heart problems taking CNS stimulants at recommended doses for ADHD. Avoid use in patients with known serious structural cardiac abnormalities, cardiomyopathy, serious heart rhythm abnormalities, coronary artery disease, and other serious heart problems. Further evaluate patients who develop exertional chest pain, unexplained syncope, or arrhythmias during Dexmethylphenidate Hydrochloride Extended-release Capsules treatment.

5.3 Blood Pressure and Heart Rate Increases

CNS stimulants cause an increase in blood pressure (mean increase approximately 2 to 4 mmHg) and heart rate (mean increase approximately 3 to 6 bpm). Individuals may have larger increases. Monitor all patients for hypertension and tachycardia.

5.4 Psychiatric Adverse Reactions

Exacerbation of Preexisting Psychosis
CNS stimulants may exacerbate symptoms of behavior disturbance and thought disorder in patients with a preexisting psychotic disorder.
Induction of a Manic Episode in Patients with Bipolar Disorder
CNS stimulants may induce a manic or mixed mood episode in patients. Prior to initiating treatment, screen patients for risk factors for developing manic episode (e.g., comorbid or history of depressive symptoms or a family history of suicide, bipolar disorder, or depression).
New Psychotic or Manic Symptoms
CNS stimulants, at recommended doses, may cause psychotic or manic symptoms (e.g., hallucinations, delusional thinking, or mania) in patients without a prior history of psychotic illness or mania. If such symptoms occur, consider discontinuing Dexmethylphenidate Hydrochloride Extended-release Capsules. In a pooled analysis of multiple short-term, placebo-controlled studies of CNS stimulants, psychotic or manic symptoms occurred in approximately 0.1% of CNS stimulant-treated patients, compared to 0 in placebo-treated patients.

5.5 Priapism

Prolonged and painful erections, sometimes requiring surgical intervention, have been reported with methylphenidate products in both pediatric and adult patients. Priapism was not reported with drug initiation but developed after some time on the drug, often subsequent to an increase in dose. Priapism has also appeared during a period of drug withdrawal (drug holidays or during discontinuation). Patients who develop abnormally sustained or frequent and painful erections should seek immediate medical attention.

5.6 Peripheral Vasculopathy, Including Raynaud's Phenomenon

CNS stimulants, including Dexmethylphenidate Hydrochloride Extended-release Capsules, used to treat ADHD are associated with peripheral vasculopathy, including Raynaud’s phenomenon. Signs and symptoms are usually intermittent and mild; however, very rare sequelae include digital ulceration and/or soft tissue breakdown. Effects of peripheral vasculopathy, including Raynaud’s phenomenon, were observed in post-marketing reports at different times and at therapeutic doses in all age groups throughout the course of treatment. Signs and symptoms generally improve after reduction in dose or discontinuation of drug. Careful observation for digital changes is necessary during treatment with ADHD stimulants. Further clinical evaluation (e.g., rheumatology referral) may be appropriate for certain patients.

5.7 Long-Term Suppression of Growth

CNS stimulants have been associated with weight loss and slowing of growth rate in pediatric patients.
In a 7-week, double-blind, placebo-controlled study of dexmethylphenidate hydrochloride extended-release capsules, the mean weight gain was greater for pediatric patients (ages 6 to 17 years) receiving placebo (+0.4 kg) than for patients receiving dexmethylphenidate hydrochloride extended-release capsules (-0.5 kg).
Careful follow-up of weight and height in pediatric patients ages 7 to 10 years who were randomized to either methylphenidate or non-medication treatment groups over 14 months, as well as in naturalistic subgroups of newly methylphenidate-treated and non-medication treated patients over 36 months (to the ages of 10 to 13 years), suggests that consistently medicated pediatric patients (i.e., treatment for 7 days per week throughout the year) have a temporary slowing in growth rate (on average, a total of about 2 cm less growth in height and 2.7 kg less growth in weight over 3 years), without evidence of growth rebound during this period of development.
Closely monitor growth (weight and height) in pediatric patients treated with CNS stimulants, including Dexmethylphenidate Hydrochloride Extended-release Capsules, and patients who are not growing or gaining height or weight as expected may need to have their treatment interrupted.

6 ADVERSE REACTIONS

The following are discussed in more detail in other sections of the labeling:

- Abuse and Dependence [see Boxed Warning, Warnings and Precautions (5.1), Drug Abuse and Dependence(9.2, 9.3)]
- Known hypersensitivity to methylphenidate or other ingredients of Dexmethylphenidate Hydrochloride Extended-release Capsules [see Contraindications (4)]
- Hypertensive Crisis with Concomitant Use of Monoamine Oxidase Inhibitors [see Contraindications (4), Drug Interactions (7.1)]
- Serious Cardiovascular Reactions [see Warnings and Precautions (5.2)]
- Blood Pressure and Heart Rate Increases [see Warnings and Precautions (5.3)]
- Psychiatric Adverse Reactions [see Warnings and Precautions (5.4)]
- Priapism [see Warnings and Precautions (5.5)]
- Peripheral Vasculopathy, including Raynaud’s Phenomenon [see Warnings and Precautions (5.6)]
- Long-Term Suppression of Growth [see Warnings and Precautions (5.7)]

6.1 Clinical Trials Experience

Because clinical trials are conducted under widely varying conditions, adverse reaction rates observed in the clinical trials of a drug cannot be directly compared to rates in the clinical trials of another drug and may not reflect the rates observed in clinical practice.

Clinical Trials Experience with Dexmethylphenidate Hydrochloride Extended-Release Capsules in Pediatric Patients with ADHD

The safety data in this section is based on data from a 7-week controlled clinical study of dexmethylphenidate hydrochloride extended-release capsules in 100 (103 randomized) pediatric patients with ADHD ages 6 to 17 years (ages 6 to 12, n = 86; ages 13 to 17, n = 17).

This study was a randomized, double-blind, placebo-controlled, parallel-group study to evaluate the time of onset, duration of efficacy, tolerability, safety of dexmethylphenidate hydrochloride extended-release capsules 5 mg to 30 mg/day who met DSM-IV criteria for ADHD [ see Clinical Studies (14.1)] .

Most Common Adverse Reactions(incidence of greater than or equal to 5% and at least twice placebo): dyspepsia, decreased appetite, headache and anxiety.

Adverse Reactions Leading to Discontinuation: 50 of 684 (7.3%) pediatric patients treated with dexmethylphenidate immediate-release tablets experienced an adverse reaction that resulted in discontinuation. The most common reasons for discontinuation were twitching (described as motor or vocal tics), anorexia, insomnia, and tachycardia (approximately 1% each).

Table 1 enumerates adverse reactions for the placebo-controlled, parallel-group study in children and adolescents with ADHD at flexible dexmethylphenidate hydrochloride extended-release capsules doses of 5–30 mg/day. The table includes only those events that occurred in 5% or more of patients treated with dexmethylphenidate hydrochloride extended-release capsules and for which the incidence in patients treated with dexmethylphenidate hydrochloride extended-release capsules was at least twice the incidence in placebo-treated patients.

Table 1: Common Adverse Reactions in Pediatric Patients (6 to 17 years of age) with ADHD
System Organ Class Adverse Reaction | Dexmethylphenidate HCl ER Capsules N=53 | Placebo N=47
Gastrointestinal Disorders | 38% | 19%
Dyspepsia | 8% | 4%
Metabolism and Nutrition Disorders | 34% | 11%
Decreased Appetite | 30% | 9%
Nervous System Disorders | 30% | 13%
Headache | 25% | 11%
Psychiatric Disorders | 26% | 15%
Anxiety | 6% | 0%
Abbreviation: attention deficit hyperactivity disorder.

Table 2 below enumerates the incidence of dose-related adverse reactions that occurred during a fixed-dose, double-blind, placebo-controlled trial in pediatric patients with ADHD taking dexmethylphenidate hydrochloride extended-release capsules up to 30 mg daily versus placebo. The table includes only those reactions that occurred in patients treated with dexmethylphenidate hydrochloride extended-release capsules for which the incidence was at least 5% and greater than the incidence among placebo-treated patients.

Table 2: Dose-Related Adverse Reactions in Pediatric Patients (6 to 17 years of age) with ADHD
System Organ Class Adverse Reaction | Dexmethylphenidate HCl ER Capsules | Dexmethylphenidate HCl ER Capsules | Dexmethylphenidate HCl ER Capsules | Placebo
System Organ Class Adverse Reaction | 10 mg/d N=64 | 20 mg/d N=60 | 30 mg/d N=58 | N=63
Gastrointestinal Disorders | 22% | 23% | 29% | 24%
Vomiting | 2% | 8% | 9% | 0%
Metabolism and Nutritional Disorders | 16% | 17% | 22% | 5%
Anorexia | 5% | 5% | 7% | 0%
Psychiatric Disorders | 19% | 20% | 38% | 8%
Insomnia | 5% | 8% | 17% | 3%
Depression | 0% | 0% | 3% | 0%
Mood Swings | 0% | 0% | 3% | 2%
Other Adverse Reactions
Irritability | 0% | 2% | 5% | 0%
Nasal Congestion | 0% | 0% | 5% | 0%
Pruritus | 0% | 0% | 3% | 0%
Abbreviation: attention deficit hyperactivity disorder.

Clinical Trials Experience With Dexmethylphenidate Hydrochloride Extended-Release Capsules in Adult Patients With ADHD

The safety data in this section is based on data from a 5-week controlled clinical study of dexmethylphenidate hydrochloride extended-release capsules in 218 adult patients (221 randomized) with ADHD ages 18 to 60 years. In this study, 101 adult patients were treated for at least 6 months.

This study was a randomized, double-blind, placebo-controlled, parallel-group study to evaluate the efficacy, safety, and tolerability of dexmethylphenidate hydrochloride extended-release capsules 20 mg, 30 mg, or 40 mg daily who met DSM-IV criteria for ADHD [ see Clinical Studies (14.2)] .

Most Common Adverse Reactions(incidence of greater than or equal to 5% and at least twice placebo): dry mouth, dyspepsia, headache, anxiety, and pharyngolaryngeal pain.

Adverse Reactions Leading to Discontinuation: During the double-blind phase of the study, 10.7% of the dexmethylphenidate hydrochloride extended-release capsules - treated patients and 7.5% of the placebo-treated patients discontinued due to adverse reactions. Three patients (1.8%) in the dexmethylphenidate hydrochloride extended-release capsules discontinued due to insomnia and jittery, respectively and two patients (1.2%) in the dexmethylphenidate hydrochloride extended-release capsules discontinued due to anorexia and anxiety, respectively.

Table 3 enumerates adverse reactions for the placebo-controlled, parallel-group study in adults with ADHD at fixed dexmethylphenidate hydrochloride extended-release capsules doses of 20, 30, and 40 mg/day. The table includes only those events that occurred in 5% or more of patients in a dexmethylphenidate hydrochloride extended-release capsules dose group and for which the incidences in patients treated with dexmethylphenidate hydrochloride extended-release capsules appeared to increase with dose.

Table 3: Dose-Related Adverse Reactions in Adult Patients (18 to 60 years of age) with ADHD
System Organ Class Adverse Reaction | Dexmethylphenidate HCl ER Capsules 20 mg N=57 | Dexmethylphenidate HCl ER Capsules 30 mg N=54 | Dexmethylphenidate HCl ER Capsules 40 mg N=54 | Placebo N=53
Gastrointestinal Disorders | 28% | 32% | 44% | 19%
Dry Mouth | 7% | 20% | 20% | 4%
Dyspepsia | 5% | 9% | 9% | 2%
Nervous System Disorders | 37% | 39% | 50% | 28%
Headache | 26% | 30% | 39% | 19%
Psychiatric Disorders | 40% | 43% | 46% | 30%
Anxiety | 5% | 11% | 11% | 2%
Respiratory, Thoracic and Mediastinal Disorders
Respiratory, Thoracic and Mediastinal Disorders | 16% | 9% | 15% | 8%
Pharyngolaryngeal Pain | 4% | 4% | 7% | 2%

Two other adverse reactions occurring in clinical trials with dexmethylphenidate hydrochloride extended-release capsules at a frequency greater than placebo, but which were not dose related were: feeling jittery (12% and 2%, respectively) and dizziness (6% and 2%, respectively).
Table 4 summarizes changes in vital signs and weight that were recorded in the adult study (N = 218) of dexmethylphenidate hydrochloride extended-release capsules in the treatment of ADHD.

Table 4: Changes (Mean ± SD) in Vital Signs and Weight by Randomized Dose During Double-Blind Treatment – Adults
 | Dexmethylphenidate HCl ER Capsules 20 mg (N= 57) | Dexmethylphenidate HCl ER Capsules 30 mg (N= 54) | Dexmethylphenidate HCl ER Capsules 40 mg (N= 54) | Placebo (N= 53)
Pulse (bpm) | 3.1 ± 11.1 | 4.3 ± 11.7 | 6.0 ± 10.1 | -1.4 ± 9.3
Diastolic BP (mmHg) | -0.2 ± 8.2 | 1.2 ± 8.9 | 2.1 ± 8.0 | 0.3 ± 7.8
Weight (kg) | -1.4 ± 2.0 | -1.2 ± 1.9 | -1.7 ± 2.3 | -0.1 ± 3.9

6.2 Post-Marketing Experience

The following additional adverse reactions have been identified during post-approval use of dexmethylphenidate. Because these reactions are reported voluntarily from a population of uncertain size, it is not always possible to reliably estimate their frequency or establish a causal relationship to drug exposure
Musculoskeletal:rhabdomyolysis
Immune System Disorders:hypersensitivity reactions, including angioedema and anaphylaxis
Adverse Reactions Reported with all Ritalin (methylphenidate) and Dexmethylphenidate Hydrochloride Formulations
The following adverse reactions associated with the use of all Ritalin (methylphenidate) and dexmethylphenidate hydrochloride formulations were identified in clinical trials, spontaneous reports, and literature. Because these reactions were reported voluntarily from a population of uncertain size, it is not always possible to estimate their frequency reliably or to establish a causal relationship to drug exposure.
Infections and Infestations:nasopharyngitis
Blood and the Lymphatic System Disorders:leukopenia, thrombocytopenia, anemia
Immune System Disorders:hypersensitivity reactions, including angioedema and anaphylaxis
Metabolism and Nutrition Disorders:decreased appetite, reduced weight gain, and suppression of growth during prolonged use in pediatric patients
Psychiatric Disorders:insomnia, anxiety, restlessness, agitation, psychosis (sometimes with visual and tactile hallucinations), depressed mood
Nervous System Disorders:headache, dizziness, tremor, dyskinesia including choreoathetoid movements, drowsiness, convulsions, cerebrovascular disorders (including vasculitis, cerebral hemorrhages and cerebrovascular accidents), serotonin syndrome in combination with serotonergic drugs
Eye Disorders:blurred vision, difficulties in visual accommodation
Cardiac Disorders:tachycardia, palpitations, increased blood pressure, arrhythmias, angina pectoris
Respiratory, Thoracic and Mediastinal Disorders:cough
Gastrointestinal Disorders:dry mouth, nausea, vomiting, abdominal pain, dyspepsia
Hepatobiliary Disorders:abnormal liver function, ranging from transaminase elevation to severe hepatic injury
Skin and Subcutaneous Tissue Disorders:hyperhidrosis, pruritus, urticaria, exfoliative dermatitis, scalp hair loss, erythema multiforme rash, thrombocytopenic purpura
Musculoskeletal and Connective Tissue Disorders:arthralgia, muscle cramps, rhabdomyolysis
Investigations:weight loss (adult ADHD patients)
Additional Adverse Reactions Reported with Other Methylphenidate Products
The list below shows adverse reactions not listed with Ritalin (methylphenidate) and dexmethylphenidate hydrochloride formulations [see Adverse Reactions (6.2)] that have been reported with other methylphenidate products based on clinical trials data and postmarketing spontaneous reports.
Blood and Lymphatic Disorders:pancytopenia
Immune System Disorders:hypersensitivity reactions such as auricular swelling, bullous conditions, eruptions, exanthemas
Psychiatric Disorders:affect lability, mania, disorientation, libido changes,
Nervous System Disorders:migraine
Eye Disorders:diplopia, mydriasis
Cardiac Disorders:sudden cardiac death, myocardial infarction, bradycardia, extrasystole, supraventricular tachycardia, ventricular extrasystole
Vascular Disorders:peripheral coldness, Raynaud's phenomenon
Respiratory, Thoracic and Mediastinal Disorders:pharyngolaryngeal pain, dyspnea
Gastrointestinal Disorders:diarrhea, constipation
Skin and Subcutaneous Tissue Disorders:angioneurotic edema, erythema, fixed drug eruption
Musculoskeletal, Connective Tissue and Bone Disorders:myalgia, muscle twitching
Renal and Urinary Disorders:hematuria
Reproductive System and Breast Disorders:gynecomastia
General Disorders:fatigue, hyperpyrexia
Urogenital Disorders:priapism

7 DRUG INTERACTIONS

7.1 Clinically Important Interactions with Dexmethylphenidate Hydrochloride Extended-Release Capsules

Table 5 presents clinically important drug interactions with Dexmethylphenidate Hydrochloride Extended-release Capsules.

Table 5: Clinically Important Drug Interactions with Dexmethylphenidate Hydrochloride Extended-Release Capsules
Monoamine Oxidase Inhibitors (MAOI)
Clinical Impact | Concomitant use of MAOIs and CNS stimulants, including Dexmethylphenidate Hydrochloride Extended-Release Capsules, can cause hypertensive crisis. Potential outcomes include death, stroke, myocardial infarction, aortic dissection, ophthalmological complications, eclampsia, pulmonary edema, and renal failure [see Contraindications (4)].
Intervention | Concomitant use of Dexmethylphenidate Hydrochloride Extended-Release Capsules with MAOIs or within 14 days after discontinuing MAOI treatment is contraindicated.
Examples | selegiline, tranylcypromine, isocarboxazid, phenelzine, linezolid, methylene blue
Antihypertensive Drugs
Clinical Impact | Dexmethylphenidate Hydrochloride Extended-Release Capsules may decrease the effectiveness of drugs used to treat hypertension [see Warnings and Precautions (5.3)].
Intervention | Monitor blood pressure and adjust the dosage of the antihypertensive drug as needed.
Examples | Potassium-sparing and thiazide diuretics, calcium channel blockers, angiotensin-converting-enzyme (ACE) inhibitors, angiotensin II receptor blockers (ARBs), beta blockers, centrally acting alpha-2 receptor agonists
Halogenated Anesthetics
Clinical Impact | Concomitant use of halogenated anesthetics and Dexmethylphenidate Hydrochloride Extended-Release Capsules may increase the risk of sudden blood pressure and heart rate increase during surgery.
Intervention | Avoid use of Dexmethylphenidate Hydrochloride Extended-Release Capsules in patients being treated with anesthetics on the day of surgery.
Examples | halothane, isoflurane, enflurane, desflurane, sevoflurane

8 USE IN SPECIFIC POPULATIONS

8.1 Pregnancy

Pregnancy Exposure Registry
There is a pregnancy exposure registry that monitors pregnancy outcomes in women exposed to ADHD medications, including Dexmethylphenidate Hydrochloride Extended-release Capsules, during pregnancy. Healthcare providers are encouraged to register patients by calling the National Pregnancy registry for ADHD medications at 1-866-961-2388 or visit https://womensmentalhealth.org/adhdmedications/.
Risk Summary
Dexmethylphenidate is the d-threoenantiomer of racemic methylphenidate. Published studies and post-marketing reports on methylphenidate use during pregnancy have not identified a drug-associated risk of major birth defects, miscarriage or adverse maternal or fetal outcomes. There may be risks to the fetus associated with the use of CNS stimulants use during pregnancy (see Clinical Considerations). Embryo-fetal development studies in rats showed delayed fetal skeletal ossification at doses up to 5 times the maximum recommended human dose (MRHD) of 20 mg/day given to adults based on plasma levels. A decrease in pup weight in males was observed in a pre- and post-natal development study with oral administration of methylphenidate to rats throughout pregnancy and lactation at doses 5 times the MRHD of 20 mg/day given to adults based on plasma levels (see Data).
The estimated background risk of major birth defects and miscarriage for the indicated population is unknown. All pregnancies have a background risk of birth defect, loss, or other adverse outcomes. In the U.S. general population, the estimated background risk of major birth defects and miscarriage in clinically recognized pregnancies is 2% to 4% and 15% to 20%, respectively.
Clinical Considerations
Fetal/Neonatal Adverse Reactions
CNS stimulants such as Dexmethylphenidate Hydrochloride Extended-release Capsules, can cause vasoconstriction and thereby decrease placental perfusion. No fetal and/or neonatal adverse reactions have been reported with the use of therapeutic doses of methylphenidate during pregnancy; however, premature delivery and low birth weight infants have been reported in amphetamine-dependent mothers.
Animal Data
In embryo-fetal development studies conducted in rats and rabbits, dexmethylphenidate was administered orally at doses of up to 20 and 100 mg/kg/day, respectively, during the period of organogenesis. No evidence of malformations was found in either the rat or rabbit study; however, delayed fetal skeletal ossification was observed at the highest dose level in rats. When dexmethylphenidate was administered to rats throughout pregnancy and lactation at doses of up to 20 mg/kg/day, postweaning body weight gain was decreased in male offspring at the highest dose, but no other effects on postnatal development were observed. At the highest doses tested, plasma levels [area under the curve (AUCs)] of dexmethylphenidate in pregnant rats and rabbits were approximately 5 and 1 times, respectively, those in adults dosed with 20 mg/day. Plasma levels in adults were comparatively similar to plasma levels in adolescents.
Racemic methylphenidate has been shown to cause malformations (increased incidence of fetal spina bifida) in rabbits when given in doses of 200 mg/kg/day throughout organogenesis.

8.2 Lactation

Risk Summary
Dexmethylphenidate is the d-threoenantiomer of racemic methylphenidate. Limited published literature, based on milk sampling from seven mothers’ reports that methylphenidate is present in human milk, which resulted in infant doses of 0.16% to 0.7% of the maternal weight-adjusted dosage and a milk/plasma ratio ranging between 1.1 and 2.7. There are no reports of adverse effects on the breastfed infant and no effects on milk production. Long-term neurodevelopmental effects on infants from stimulant exposure are unknown. The developmental and health benefits of breastfeeding should be considered along with the mother’s clinical need for Dexmethylphenidate Hydrochloride Extended-release Capsules and any potential adverse effects on the breastfed infant from Dexmethylphenidate Hydrochloride Extended-release Capsules or from the underlying maternal condition.
Clinical Considerations
Monitor breastfeeding infants for adverse reactions, such as agitation, insomnia, anorexia, and reduced weight gain.

8.4 Pediatric Use

The safety and effectiveness of dexmethylphenidate hydrochloride extended-release capsules in pediatric patients less than 6 years have not been established.
The safety and effectiveness of dexmethylphenidate hydrochloride extended-release capsules for the treatment of ADHD have been established in pediatric patients ages 6 to 17 years in two adequate and well-controlled clinical trials [see Clinical Studies (14.2)] . The long-term efficacy of dexmethylphenidate hydrochloride extended-release capsules in pediatric patients has not been established.
Long Term Suppression of Growth
Growth should be monitored during treatment with stimulants, including Dexmethylphenidate Hydrochloride Extended-release Capsules. Pediatric patients who are not growing or gaining weight as expected may need to have their treatment interrupted [see Warnings and Precautions (5.7)] .
Juvenile Animal Toxicity Data
Rats treated with racemic methylphenidate early in the postnatal period through sexual maturation demonstrated a decrease in spontaneous locomotor activity in adulthood. A deficit in acquisition of a specific learning task was observed in females only. The doses at which these findings were observed are at least 6 times the MRHD of 60 mg/day given to children on a mg/m^2basis.
In a study conducted in young rats, racemic methylphenidate was administered orally at doses of up to 100 mg/kg/day for 9 weeks, starting early in the postnatal period (postnatal Day 7) and continuing through sexual maturity (postnatal Week 10). When these animals were tested as adults (postnatal Weeks 13 to14), decreased spontaneous locomotor activity was observed in males and females previously treated with 50 mg/kg/day (approximately 4 times the MRHD of 60 mg/day of racemic methylphenidate given to children on a mg/m^2basis) or greater, and a deficit in the acquisition of a specific learning task was seen in females exposed to the highest dose (8 times the MRHD given to children on a mg/m^2basis). The no effect level for juvenile neurobehavioral development in rats was 5 mg/kg/day (approximately 0.5 times the MRHD given to children on a mg/m^2basis). The clinical significance of the long-term behavioral effects observed in rats is unknown.

8.5 Geriatric Use

Dexmethylphenidate hydrochloride extended-release capsules have not been studied in the geriatric population.

9 DRUG ABUSE AND DEPENDENCE

9.1 Controlled Substance

Dexmethylphenidate Hydrochloride Extended-release Capsules contains dexmethylphenidate hydrochloride, a Schedule II controlled substance.

9.2 Abuse

CNS stimulants, including Dexmethylphenidate Hydrochloride Extended-release Capsules, other methylphenidate-containing products, and amphetamines have a high potential for abuse. Abuse is characterized by impaired control over drug use despite harm, and craving.
Signs and symptoms of CNS stimulant abuse include increased heart rate, respiratory rate, blood pressure, and/or sweating, dilated pupils, hyperactivity, restlessness, insomnia, decreased appetite, loss of coordination, tremors, flushed skin, vomiting, and/or abdominal pain. Anxiety, psychosis, hostility, aggression, suicidal or homicidal ideation have also been observed. Abusers of CNS stimulants may chew, snort, inject, or use other unapproved routes of administration which may result in overdose and death [see Overdosage (10)] .
To reduce the abuse of CNS stimulants including Dexmethylphenidate Hydrochloride Extended-release Capsules, assess the risk of abuse prior to prescribing. After prescribing, keep careful prescription records, educate patients and their families about abuse and on proper storage and disposal of CNS stimulants [see How Supplied/Storage and Handling (16)] , monitor for signs of abuse while on therapy, and reevaluate the need for Dexmethylphenidate Hydrochloride Extended-release Capsules use.

9.3 Dependence

Tolerance
Tolerance (a state of adaptation in which exposure to a drug results in a reduction of the drug’s desired and/or undesired effects over time) can occur during chronic therapy with CNS stimulants, including Dexmethylphenidate Hydrochloride Extended-release Capsules.
Dependence
Physical dependence (which is manifested by a withdrawal syndrome produced by abrupt cessation, rapid dose reduction, or administration of an antagonist) may occur in patients treated with CNS stimulants including Dexmethylphenidate Hydrochloride Extended-release Capsules. Withdrawal symptoms after abrupt cessation following prolonged high-dosage administration of CNS stimulants include dysphoric mood; fatigue; vivid, unpleasant dreams; insomnia or hypersomnia; increased appetite; and psychomotor retardation or agitation.

10 OVERDOSAGE

Human Experience
Signs and symptoms of acute methylphenidate overdosage, resulting principally from overstimulation of the CNS and from excessive sympathomimetic effects, may include the following: nausea, vomiting, diarrhea, restlessness, anxiety, agitation, tremors, hyperreflexia, muscle twitching, convulsions (may be followed by coma), euphoria, confusion, hallucinations, delirium, sweating, flushing, headache, hyperpyrexia, tachycardia, palpitations, cardiac arrhythmias, hypertension, hypotension, tachypnea, mydriasis, and dryness of mucous membranes, and rhabdomyolysis.
Overdose Management
Consult with a Certified Poison Control Center (1-800-222-1222) for the latest recommendations.

11 DESCRIPTION

Dexmethylphenidate Hydrochloride Extended-release Capsules contains dexmethylphenidate hydrochloride, a CNS stimulant. Dexmethylphenidate hydrochloride is the d-threoenantiomer of racemic methylphenidate hydrochloride. Dexmethylphenidate Hydrochloride Extended-release Capsules is an extended-release formulation of dexmethylphenidate with a bi-modal release profile. Each bead-filled dexmethylphenidate hydrochloride extended-release capsule contains half the dose as immediate-release beads and half as enteric-coated, delayed-release beads, thus providing an immediate release of dexmethylphenidate and a delayed release of dexmethylphenidate. Dexmethylphenidate Hydrochloride Extended-release Capsules is intended for oral administration and is available as 15 mg and 30 mg extended-release capsules.
Chemically, dexmethylphenidate hydrochloride is methyl α-phenyl-2-piperidineacetate hydrochloride, (R,R’)-(+)-. Its molecular formula is C14H19NO2•HCl. Its structural formula is:

Note* = asymmetric carbon center

Dexmethylphenidate hydrochloride is a white to off-white powder. Its solutions are acid to litmus. It is freely soluble in water and in methanol, soluble in alcohol, and slightly soluble in chloroform and in acetone. Its molecular weight is 269.77 g/mol.

Inactive ingredients:sugar spheres, methacrylic acid copolymers, triethyl citrate, talc, colloidal silicon dioxide, Hypromellose, polydextrose, triacetin, macrogol/PEG, FD&C Yellow #6/Sunset Yellow FCF AL, FD&C Blue #2/ indigo carmine AL, titanium dioxide and gelatin.

12 CLINICAL PHARMACOLOGY

12.1 Mechanism of Action

Dexmethylphenidate hydrochloride is a central nervous system (CNS) stimulant. The mode of therapeutic action in ADHD is not known.

12.2 Pharmacodynamics

Dexmethylphenidate is the more pharmacologically active d-enantiomer of racemic methylphenidate. Methylphenidate blocks the reuptake of norepinephrine and dopamine into the presynaptic neuron and increase the release of these monoamines into the extraneuronal space.
Cardiac Electrophysiology
At the recommended maximum total daily dosage of 40 mg, dexmethylphenidate hydrochloride extended-release capsules does not prolong the QTc interval to any clinically relevant extent.

12.3 Pharmacokinetics

Absorption
Dexmethylphenidate hydrochloride extended-release capsules produces a bi-modal plasma concentration-time profile (i.e., 2 distinct peaks approximately 4 hours apart) when orally administered to healthy adults. The initial rate of absorption for dexmethylphenidate hydrochloride extended-release capsules is similar to that of dexmethylphenidate hydrochloride tablets as shown by the similar rate parameters between the 2 formulations, i.e., first peak concentration (Cmax1), and time to the first peak (tmax1), which is reached in 1.5 hours (typical range 1 to 4 hours). The mean time to the interpeak minimum (tminip) is slightly shorter, and time to the second peak (tmax2) is slightly longer for dexmethylphenidate hydrochloride extended-release capsules given once daily (about 6.5 hours, range 4.5 to 7 hours) compared to dexmethylphenidate hydrochloride tablets given in 2 doses 4 hours apart (see Figure 1), although the ranges observed are greater for dexmethylphenidate hydrochloride extended-release capsules.
Dexmethylphenidate hydrochloride extended-release capsules given once daily exhibits a lower second peak concentration (Cmax2), higher interpeak minimum concentrations (Cminip), and fewer peak and trough fluctuations than dexmethylphenidate hydrochloride tablets given in 2 doses given 4 hours apart. This is due to an earlier onset and more prolonged absorption from the delayed-release beads (see Figure 1).
The ratio of geometric mean of AUC(0-inf)and Cmaxafter administration of dexmethylphenidate hydrochloride extended-release capsules given once daily are 1.02 and 0.86 respectively, to the same total dose of dexmethylphenidate hydrochloride tablets given in 2 doses 4 hours apart. The variability in Cmax, Cmin, and AUC is similar between dexmethylphenidate hydrochloride extended-release capsules and dexmethylphenidate hydrochloride immediate-release tablets with approximately a 3-fold range in each.
Approximately 90% of the dose is absorbed after oral administration of radiolabeled racemic methylphenidate. However, due to first pass metabolism the mean absolute bioavailability of dexmethylphenidate when administered in various formulations was 22% to 25%.
Figure 1. Mean Dexmethylphenidate Plasma Concentration-Time Profiles After Administration of 1 x 20 mg Dexmethylphenidate Hydrochloride Extended-Release Capsules (n=24) and 2 x 10 mg Dexmethylphenidate Hydrochloride Immediate-Release Tablets Tablets (n=25)

After single dose administration, dexmethylphenidate hydrochloride extended-release capsules demonstrated dose proportional PK in the range of 5 mg to 40 mg.
For patients unable to swallow the capsule, the contents may be sprinkled on applesauce and administered [see Dosage and Administration (2)] .
Distribution
The plasma protein binding of dexmethylphenidate is not known; racemic methylphenidate is bound to plasma proteins by
12% to 15%, independent of concentration. Dexmethylphenidate shows a volume of distribution of 2.65 ± 1.11 L/kg.
Elimination
Plasma dexmethylphenidate concentrations decline monophasically following oral administration of dexmethylphenidate hydrochloride extended-release capsules. The mean terminal elimination half-life of dexmethylphenidate was about 3 hours in healthy adults. Pediatric patients tend to have slightly shorter half-lives with means of 2 to 3 hours. Dexmethylphenidate was eliminated with a mean clearance of 0.40 ± 0.12 L/hr/kg after intravenous administration.
Metabolism
In humans, dexmethylphenidate is metabolized primarily via de-esterification to d-α-phenyl-piperidine acetic acid (also known as d-ritalinic acid). This metabolite has little or no pharmacological activity. There is no in vivo interconversion to the l-threo-enantiomer.
Excretion
After oral dosing of radiolabeled racemic methylphenidate in humans, about 90% of the radioactivity was recovered in urine. The main urinary metabolite of racemic (d,l-)methylphenidate was d,l-ritalinic acid, accountable for approximately 80% of the dose. Urinary excretion of parent compound accounted for 0.5% of an intravenous dose.
Studies in Specific Populations
Male and Female Patients
After administration of dexmethylphenidate hydrochloride extended-release capsules, the first peak, (Cmax1) was on average 45% higher in women. The interpeak minimum and the second peak also tended to be slightly higher in women although the difference was not statistically significant, and these patterns remained even after weight normalization.
Racial or Ethnic Groups
There is insufficient experience with the use of dexmethylphenidate hydrochloride extended-release capsules to detect ethnic variations in pharmacokinetics.
Pediatric Patients
The pharmacokinetics of dexmethylphenidate after dexmethylphenidate hydrochloride extended-release capsules administration have not been studied in pediatrics less than 18 years of age. When a similar formulation of racemic methylphenidate was examined in 15 patients between 10 and 12 years of age and 3 patients with ADHD between 7 and 9 years of age, the time to the first peak was similar, although the time until the between peak minimum, and the time until the second peak were delayed and more variable in pediatric patients compared to adults. After administration of the same dose to pediatric patients and adults, concentrations in pediatric patients were approximately twice the concentrations observed in adults. This higher exposure is almost completely due to smaller body size as no relevant age-related differences in dexmethylphenidate pharmacokinetic parameters (i.e., clearance and volume of distribution) are observed after normalization to dose and weight.
Patients with Renal Impairment
There is no experience with the use of dexmethylphenidate hydrochloride extended-release capsules in patients with renal impairment. Since renal clearance is not an important route of methylphenidate elimination, renal impairment is expected to have little effect on the pharmacokinetics of dexmethylphenidate hydrochloride extended-release capsules.
Patients with Hepatic Impairment
There is no experience with the use of dexmethylphenidate hydrochloride extended-release capsules in patients with hepatic impairment.
Drug Interaction Studies
Methylphenidate is not metabolized by cytochrome P450 (CYP) isoenzymes to a clinically relevant extent. Inducers or inhibitors of CYPs are not expected to have any relevant impact on methylphenidate pharmacokinetics. Conversely, the d- and l-enantiomers of methylphenidate did not relevantly inhibit CYP1A2, 2C8, 2C9, 2C19, 2D6, 2E1 or 3A. Clinically, methylphenidate coadministration did not increase plasma concentrations of the CYP2D6 substrate desipramine.

13 NONCLINICAL TOXICOLOGY

13.1 Carcinogenesis, Mutagenesis, and Impairment of Fertility

Carcinogenesis
Lifetime carcinogenicity studies have not been carried out with dexmethylphenidate. In a lifetime carcinogenicity study carried out in B6C3F1 mice, racemic methylphenidate caused an increase in hepatocellular adenomas, and in males only, an increase in hepatoblastomas was seen at a daily dose of approximately 60 mg/kg/day. This dose is approximately 2-times the maximum recommended human dose (MRHD) of 60 mg/day of racemic methylphenidate given to children on a mg/m^2basis. Hepatoblastoma is a relatively rare rodent malignant tumor type. There was no increase in total malignant hepatic tumors. The mouse strain used is sensitive to the development of hepatic tumors, and the significance of these results to humans is unknown.
Racemic methylphenidate did not cause any increase in tumors in a lifetime carcinogenicity study carried out in F344 rats; the highest dose used was approximately 45 mg/kg/day, which is approximately 4 times the MRHD (children) of 60 mg/day of racemic methylphenidate in children on a mg/m^2basis.
In a 24-week carcinogenicity study with racemic methylphenidate in the transgenic mouse strain p53+/-, which is sensitive to genotoxic carcinogens, there was no evidence of carcinogenicity. Male and female mice were fed diets containing the same concentrations as in the lifetime carcinogenicity study; the high-dose group was exposed to 60 to 74 mg/kg/day of racemic methylphenidate.
Mutagenesis
Dexmethylphenidate was not mutagenic in the in vitroAmes reverse mutation assay, in the in vitromouse lymphoma cell forward mutation assay, or in the in vivomouse bone marrow micronucleus test. In an in vitroassay using cultured Chinese Hamster Ovary (CHO) cells treated with racemic methylphenidate, sister chromatid exchanges and chromosome aberrations were increased, indicative of a weak clastogenic response.
Impairment of Fertility
No human data on the effect of methylphenidate on fertility are available.
Fertility studies have not been conducted with dexmethylphenidate. Racemic methylphenidate did not impair fertility in male or female mice that were fed diets containing the drug in an 18-week continuous breeding study. The study was conducted at doses of up to 160 mg/kg/day, approximately 10-times the maximum recommended human dose of 60 mg/day of racemic methylphenidate given to adolescents on a mg/m^2basis.

14 CLINICAL STUDIES

14.1 Pediatric Patients

A randomized, double-blind, placebo-controlled, parallel-group study (Study 1) was conducted in 103 pediatric patients (ages 6 to 12, n = 86; ages 13 to 17, n = 17) who met DSM-IV criteria for ADHD inattentive, hyperactive-impulsive or combined inattentive/hyperactive-impulsive subtypes (Study 1).
Patients were randomized to receive either a flexible-dose of dexmethylphenidate hydrochloride extended-release capsules (5 to 30 mg/day) or placebo once daily for 7 weeks. During the first 5 weeks of treatment patients were titrated to their optimal dose and remained on this optimal dose for the last 2 weeks of the study without dose changes or interruption.
Signs and symptoms of ADHD were evaluated by comparing the mean change from baseline to endpoint for dexmethylphenidate hydrochloride extended-release capsules and placebo-treated patients using an intent-to-treat analysis of the primary efficacy outcome measure, the DSM-IV total subscale score of the Conners ADHD/DSM-IV Scales for teachers (CADS-T). The CADS-T includes the ADHD Index (12 items) and the DSM-IV total subscale (18 items, total score range: 0 to 54); the latter is divided into inattentive (9 items) and hyperactive-impulsive (9 items) subscales. Teachers assessed behavior observed during the school day by completing the CADS-T weekly. A decrease in the CADS-T DSM-IV total subscale score from baseline indicates improvement.
The CADS-T total scores showed a statistically significant treatment effect in favor of dexmethylphenidate hydrochloride extended-release capsules than placebo Table (6). There were insufficient adolescents enrolled in this study to assess the efficacy for dexmethylphenidate hydrochloride extended-release capsules in the adolescent population. However, pharmacokinetic considerations and evidence of effectiveness of dexmethylphenidate hydrochloride immediate-release tablets in adolescents support the effectiveness of dexmethylphenidate hydrochloride extended-release capsules in this population.

Table 6: Summary of Efficacy Results from ADHD Study in Pediatric Patients (6 – 17 years) (Study 1)
Study Number | Treatment Group | Primary Efficacy Measure: CADS-T Total Score
Study Number | Treatment Group | Mean Baseline Score (SD) | LS Mean Change from Baseline (SE) | Placebo-subtracted Differencea (95% CI)
Study 1 | Dexmethylphenidate HCl ER Capsules 5-30 mg/day (n = 52) | 33.3 (9.18) | 16.41 (1.8) | 10.64 (5.38, 15.91)
Study 1 | Placebo (n = 45) | 34.9 (10.03) | 5.77 (1.93) | --
Abbreviations: ADHD, Attention Deficit Hyperactivity Disorder; SD, standard deviation; SE, standard error; LS Mean, least-squares mean; CI, confidence interval, not adjusted for multiple comparisons.
aDifference (drug minus placebo) in least-squares mean change from baseline.

In 2 additional cross-over studies (Studies 2 and 3) in pediatric patients ages 6 to 12 years who received 20 mg dexmethylphenidate hydrochloride extended-release capsules or placebo, dexmethylphenidate hydrochloride extended-release capsules was found to have a statistically significant treatment effect versus placebo on the Swanson, Kotkin, Agler, M-Flynn & Pelham (SKAMP) rating scale total scores at all time points after dosing in each study (0.5, 1, 3, 4, 5, 7, 9, 10, 11 and 12 hours in Study 2 and 1, 2, 4, 6, 8, 9, 10, 11 and 12 hours in Study 3). SKAMP is a validated 13-item teacher-rated scale that assesses manifestations of ADHD in a classroom setting. A treatment effect was also observed 0.5 hours after administration of dexmethylphenidate hydrochloride extended-release capsules 20 mg in an additional study of ADHD patients ages 6 to 12 years.

14.2 Adult Patients

A randomized, double-blind, placebo-controlled, parallel-group (Study 4) was conducted in 221 adult patients ages 18 to 60 years who met DSM-IV criteria for ADHD inattentive, hyperactive impulsive or combined inattentive/hyperactive-impulsive subtypes (Study 4).
Patients were randomized to receive either a fixed dose of dexmethylphenidate hydrochloride extended-release capsules (20, 30, or 40 mg/day) or placebo once daily for 5 weeks. Patients randomized to dexmethylphenidate hydrochloride extended-release capsules were initiated on a 10 mg/day starting dose and titrated in increments of 10 mg/week to the randomly assigned fixed dose. Patients were maintained on their fixed dose (20, 30 or 40 mg/day) for a minimum of 2 weeks.
Signs and symptoms of ADHD were evaluated by comparing the mean change from baseline to endpoint for dexmethylphenidate hydrochloride extended-release capsules and placebo-treated patients using an intent-to-treat analysis of the primary efficacy outcome measure, the investigator-administered DSM-IV Attention-Deficit/Hyperactivity Disorder Rating Scale (DSM-IV ADHD RS).
The DSM-IV ADHD-RS is an 18-item questionnaire with a score range of 0 to 54 points that measures the core symptoms of ADHD and includes both hyperactive/impulsive and inattentive subscales.
All 3 dexmethylphenidate hydrochloride extended-release capsules doses (20, 30, and 40 mg/day) showed a statistically significantly treatment effect compared to placebo. There was no obvious increase in effectiveness with increasing the dose.

Table 7: Summary of Efficacy Results from ADHD Study in Adults (Study 4)
Study Number | Treatment Group | Primary Efficacy Measure: ADHD-RS Total Score
Study Number | Treatment Group | Mean Baseline Score (SD) | LS Mean Change from Baseline (SE) | Placebo-subtracted Differencea (95% CI)
Study 4 | Dexmethylphenidate HCl ER Capsules 20 mg/day (n = 57) | 36.8 (7.2) | 13.27 (1.44) | 5.71 (1.64, 9.78)
Study 4 | Dexmethylphenidate HCl ER Capsules 30 mg/day (n = 54) | 36.9 (8.07) | 12.86 (1.48) | 5.31 (1.18, 9.44)
Study 4 | Dexmethylphenidate HCl ER Capsules 40 mg/day (n = 54) | 36.9 (8.25) | 16.51 (1.48) | 8.96 (4.83, 13.08)
Study 4 | Placebo (n = 53) | 37.5 (7.82) | 7.55 (1.49) | --
Abbreviations: ADHD, Attention Deficit Hyperactivity Disorder; SD, standard deviation; SE, standard error; LS Mean, least-squares mean; CI, confidence interval, not adjusted for multiple comparisons.
aDifference (drug minus placebo) in least-squares mean change from baseline.

16 HOW SUPPLIED/STORAGE AND HANDLING

Dexmethylphenidate Hydrochloride Extended-release Capsules are available as follows:
15 mg capsules – white opaque cap and body, imprinted in black ink “par” on cap and “428” on body; supplied in bottles of 100 (NDC 49884-428-01) and 1000 (NDC 49884-428-10).
30 mg capsules – white opaque cap and body, imprinted in green ink “par” on cap and “430” on body; supplied in bottles of 100 (NDC 49884-430-01) and 1000 (NDC 49884-430-10).
Store at 20°C to 25°C (68°F to 77°F); excursions permitted between 15°C to 30°C (59°F to 86°F) [see USP Controlled Room Temperature].
Dispense in tight container (USP).
Disposal
Comply with local laws and regulations on drug disposal of CNS stimulants. Dispose of remaining, unused, or expired Dexmethylphenidate Hydrochloride Extended-release Capsules by a medicine takeback program or by an authorized collector registered with the Drug Enforcement Administration. If no take-back program or authorized collector is available, mix Dexmethylphenidate Hydrochloride Extended-release Capsules with an undesirable, non-toxic substance to make it less appealing to children and pets. Place the mixture in a container such as a sealed plastic bag and discard Dexmethylphenidate Hydrochloride Extended-release Capsules in the household trash.

17 PATIENT COUNSELING INFORMATION

Advise patients to read the FDA-approved patient labeling (Medication Guide).
Controlled Substance Status/High Potential for Abuse and Dependence
Advise patients that Dexmethylphenidate Hydrochloride Extended-release Capsules is a controlled substance, and it can be abused and lead to dependence. Instruct patients that they should not give Dexmethylphenidate Hydrochloride Extended-release Capsules to anyone else. Advise patients to store Dexmethylphenidate Hydrochloride Extended-release Capsules in a safe place, preferably locked, to prevent abuse. Advise patients to comply with laws and regulations on drug disposal. Advise patients to dispose of remaining, unused, or expired Dexmethylphenidate Hydrochloride Extended-release Capsules by a medicine take-back program if available [see Boxed Warning, Warnings and Precautions (5.1), Drug Abuse and Dependence(9.1, 9.2, 9.3), How Supplied/Storage and Handling (16)] .
Serious Cardiovascular Risks
Advise patients that there is a potential serious cardiovascular risk including sudden death, myocardial infarction, stroke, and hypertension with Dexmethylphenidate Hydrochloride Extended-release Capsules use. Instruct patients to contact a healthcare provider immediately if they develop symptoms such as exertional chest pain, unexplained syncope, or other symptoms suggestive of cardiac disease [see Warnings and Precautions (5.2)] .
Blood Pressure and Heart Rate Increases
Instruct patients that Dexmethylphenidate Hydrochloride Extended-release Capsules can cause elevations of their blood pressure and pulse rate [see Warnings and Precautions (5.3)] .
Psychiatric Risks
Advise patients that Dexmethylphenidate Hydrochloride Extended-release Capsules, at recommended doses, can cause psychotic or manic symptoms, even in patients without prior history of psychotic symptoms or mania [see Warnings and Precautions (5.4)] .
Priapism
Advise patients of the possibility of painful or prolonged penile erections (priapism). Instruct them to seek immediate medical attention in the event of priapism [see Warnings and Precautions (5.5)] .
Circulation Problems in Fingers and Toes (Peripheral Vasculopathy, Including Raynaud’s Phenomenon)
Instruct patients beginning treatment with Dexmethylphenidate Hydrochloride Extended-release Capsules about the risk of peripheral vasculopathy, including Raynaud’s phenomenon, and associated signs and symptoms: fingers or toes may feel numb, cool, painful, and/or may change color from pale, to blue, to red. Instruct patients to report to their physician any new numbness, pain, skin color change, or sensitivity to temperature in fingers or toes.
Instruct patients to call their physician immediately with any signs of unexplained wounds appearing on fingers or toes while taking Dexmethylphenidate Hydrochloride Extended-release Capsules. Further clinical evaluation (e.g., rheumatology referral) may be appropriate for certain patients [see Warnings and Precautions (5.6)] .
Suppression of Growth
Advise patients that Dexmethylphenidate Hydrochloride Extended-release Capsules may cause slowing of growth and weight loss [see Warnings and Precautions (5.7)] .
Pregnancy Registry
Advise patients that there is a pregnancy exposure registry that monitors pregnancy outcomes in patients exposed to ADHD medications, including Dexmethylphenidate Hydrochloride Extended-release Capsules, during pregnancy [see Use in Specific Populations (8.1)] .
Manufactured by:
Par Pharmaceutical
Chestnut Ridge, NY 10977 U.S.A
Under License from:
Intellipharmaceutics Corp.
Toronto, Ontario M9W 5X2 CANADA

MEDICATION GUIDE

Dexmethylphenidate (dex meth ill FEN i date) Hydrochloride
Extended-Release Capsules CII

What is the most important information I should know about Dexmethylphenidate Hydrochloride Extended-Release Capsules?
Dexmethylphenidate Hydrochloride Extended-Release Capsules is a federal controlled substance (CII) because it can be abused or lead to dependence. Keep Dexmethylphenidate Hydrochloride Extended-Release Capsules in a safe place to prevent misuse and abuse. Selling or giving away Dexmethylphenidate Hydrochloride Extended-Release Capsules may harm others, and is against the law.
Tell your doctor if you or your child have abused or been dependent on alcohol, prescription medicines or street drugs.
The following have been reported with use of methylphenidate hydrochloride and other stimulant medicines:
1. Heart-related problems:

- sudden death in patients who have heart problems or heart defects
- stroke and heart attack in adults
- increased blood pressure and heart rate

Tell your doctor if you or your child have any heart problems, heart defects, high blood pressure, or a family history of these problems.
Your doctor should check you or your child carefully for heart problems before starting Dexmethylphenidate Hydrochloride Extended-Release Capsules.
Your doctor should check you or your child’s blood pressure and heart rate regularly during treatment with Dexmethylphenidate Hydrochloride Extended-Release Capsules.
Call your doctor right away if you or your child has any signs of heart problems such as chest pain, shortness of breath, or fainting while taking Dexmethylphenidate Hydrochloride Extended-Release Capsules.
2. Mental (Psychiatric) problems:
All patients

- new or worse behavior and thought problems
- new or worse bipolar illness
- new or worse aggressive behavior or hostility
- new psychotic symptoms (such as hearing voices, believing things that are not true, are suspicious) or new manic symptoms

Tell your doctor about any mental problems you or your child have, or about a family history of suicide, bipolar illness, or depression.
Call your doctor right away if you or your child have any new or worsening mental symptoms or problems while taking Dexmethylphenidate Hydrochloride Extended-Release Capsules, especially seeing or hearing things that are not real, believing things that are not real, or are suspicious.

What Is Dexmethylphenidate Hydrochloride Extended-Release Capsules?

- Dexmethylphenidate Hydrochloride Extended-Release Capsules is a central nervous system stimulant (CNS) prescription medicine. It is used for the treatment of Attention-Deficit Hyperactivity Disorder (ADHD).Dexmethylphenidate Hydrochloride Extended-Release Capsules may help increase attention and decrease impulsiveness and hyperactivity in patients with ADHD.
- Dexmethylphenidate Hydrochloride Extended-Release Capsules should be used as a part of a total treatment program for ADHD that may include counseling or other therapies.

Who should not take Dexmethylphenidate Hydrochloride Extended-Release Capsules?
Dexmethylphenidate Hydrochloride Extended-Release Capsules should not be taken if you or your child:

- are allergic to methylphenidate hydrochloride, or any of the ingredients in Dexmethylphenidate Hydrochloride Extended-Release Capsules. See the end of this Medication Guide for a complete list of ingredients in Dexmethylphenidate Hydrochloride Extended-Release Capsules.
- are taking or have taken within the past 14 days an anti-depression medicine called a monoamine oxidase inhibitor or MAOI.

Dexmethylphenidate Hydrochloride Extended-Release Capsules may not be right for you or your child. Before starting Dexmethylphenidate Hydrochloride Extended-Release Capsules tell your or your child’s doctor about all health conditions (or a family history of) including:

- heart problems, heart defects, high blood pressure
- mental problems including psychosis, mania, bipolar illness, or depression
- circulation problems in fingers or toes
- if you are pregnant or plan to become pregnant. It is not known if Dexmethylphenidate Hydrochloride Extended-Release Capsules will harm your unborn baby.

o There is a pregnancy registry for females who are exposed to ADHD medications, including Dexmethylphenidate Hydrochloride Extended-Release Capsules, during pregnancy. The purpose of the registry is to collect information about the health of females exposed to Dexmethylphenidate Hydrochloride Extended-Release Capsules and their baby. If you or your child becomes pregnant during treatment with Dexmethylphenidate Hydrochloride Extended-Release Capsules, talk to your healthcare provider about registering with the National Pregnancy Registry of ADHD medications at 1-866-961-2388 or visit online at https://womensmentalhealth.org/adhd-medications/.

- if you are breastfeeding or plan to breastfeed. Dexmethylphenidate hydrochloride passes into your breast milk. Talk to your healthcare provider about the best way to feed the baby during treatment with Dexmethylphenidate Hydrochloride Extended-Release Capsules.

Tell your doctor about all of the medicines that you or your child takes including prescription and over-the-counter medicines, vitamins, and herbal supplements.Dexmethylphenidate Hydrochloride Extended-Release Capsules and some medicines may interact with each other and cause serious side effects. Sometimes the doses of other medicines will need to be adjusted while taking Dexmethylphenidate Hydrochloride Extended-Release Capsules.
Your doctor will decide whether Dexmethylphenidate Hydrochloride Extended-Release Capsules can be taken with other medicines.

Especially tell your doctor if you or your child takes:

- anti-depression medicines including MAOIs
- blood pressure medicines (anti-hypertensive)

Know the medicines that you or your child takes. Keep a list of your medicines with you to show your doctor and pharmacist.

- You should not take Dexmethylphenidate Hydrochloride Extended-Release Capsules on the day of your operation if a certain type of anesthetic is used. This is because there is a chance of a sudden rise in blood pressure and heart rate during the operation.

Do not start any new medicine while taking Dexmethylphenidate Hydrochloride Extended-Release Capsules without talking to your doctor first.

How should Dexmethylphenidate Hydrochloride Extended-Release Capsules be taken?

- Take Dexmethylphenidate Hydrochloride Extended-Release Capsules exactly as prescribed. Your doctor may adjust the dose until it is right for you or your child.
- Take Dexmethylphenidate Hydrochloride Extended-Release Capsules once each day in the morning. Dexmethylphenidate Hydrochloride Extended-Release Capsules is an extended-release capsule.
- Dexmethylphenidate Hydrochloride Extended-Release Capsules can be taken with or without food. Taking Dexmethylphenidate Hydrochloride Extended-Release Capsules with food may slow the time it takes for the medicine to start working.
- Swallow Dexmethylphenidate Hydrochloride Extended-Release Capsules whole with water or other liquids. Do not chew, crush, or divide the capsules or the beads in the capsule.If you or your child cannot swallow the capsule, open it and sprinkle the small beads of medicine over a spoonful of applesauce and swallow it right away without chewing.
- From time to time, your doctor may stop Dexmethylphenidate Hydrochloride Extended-Release Capsules treatment for a while to check ADHD symptoms.
- Your doctor may do regular checks of the blood, heart, and blood pressure while taking Dexmethylphenidate Hydrochloride Extended-Release Capsules.
- Children should have their height and weight checked often while taking Dexmethylphenidate Hydrochloride Extended-Release Capsules. Dexmethylphenidate Hydrochloride Extended-Release Capsules treatment may be stopped if a problem is found during these check-ups.
- In case of poisoning call your poison control center at 1-800-222-1222 right away, or go to the nearest hospital emergency room.

What are the possible side effects of Dexmethylphenidate Hydrochloride Extended-Release Capsules?
Dexmethylphenidate Hydrochloride Extended-Release Capsules may cause serious side effects, including:

- See “What is the most important information I should know about Dexmethylphenidate Hydrochloride Extended-Release Capsules?”for information on reported heart and mental problems.
- painful and prolonged erections (priapism)have occurred with methylphenidate. If you or your child develops priapism, seek medical help right away. Because of the potential for lasting damage, priapism should be evaluated by a doctor immediately.
- circulation problems in fingers and toes(Peripheral Vasculopathy, including Raynaud’s phenomenon):
  - fingers or toes may feel numb, cool, painful
  - fingers or toes may change color from pale, to blue, to red

Tell your doctor if you or your child have, numbness, pain, skin color change, or sensitivity to temperature in the fingers or toes.

- Call your doctor right away if you have or your child has any signs of unexplained wounds appearing on fingers or toes while taking Dexmethylphenidate Hydrochloride Extended-Release Capsules.
- slowing of growth (height and weight) in children

Common side effects include:
Children (6 - 17 years)
• dyspepsia • decreased appetite • headache • anxiety
Adults
• dry mouth • dyspepsia • headache • anxiety • pharyngolaryngeal pain
Call your doctor for medical advice about side effects. You may report side effects to FDA at 1-800-FDA-1088.

How should I store Dexmethylphenidate Hydrochloride Extended-Release Capsules?

- Store Dexmethylphenidate Hydrochloride Extended-Release Capsules in a safe place and in a tightly closed container at room temperature between 68°F to 77°F (20°C to 25°C).
- Dispose of remaining, unused, or expired Dexmethylphenidate Hydrochloride Extended-Release Capsules by a medicine take-back program at authorized collection sites such as retail pharmacies, hospital or clinic pharmacies, and law enforcement locations. If no take-back program or authorized collector is available, mix Dexmethylphenidate Hydrochloride Extended-Release Capsules with an undesirable, nontoxic substance such as dirt, cat litter, or used coffee grounds to make it less appealing to children and pets. Place the mixture in a container such as a sealed plastic bag and throw away (discard) Dexmethylphenidate Hydrochloride Extended-Release Capsules in the household trash.
- Keep Dexmethylphenidate Hydrochloride Extended-Release Capsules and all medicines out of the reach of children.

General information about the safe and effective use of Dexmethylphenidate Hydrochloride Extended-Release Capsules.
Medicines are sometimes prescribed for purposes other than those listed in a Medication Guide. You can ask your pharmacist or doctor for information about Dexmethylphenidate Hydrochloride Extended-Release Capsules that is written for healthcare professionals. Do not use Dexmethylphenidate Hydrochloride Extended-Release Capsules for a condition for which it was not prescribed. Do not give Dexmethylphenidate Hydrochloride Extended-Release Capsules to other people, even if they have the same symptoms that you have. It may harm them and it is against the law.

What are the ingredients in Dexmethylphenidate Hydrochloride Extended-Release Capsules?
Active Ingredient:dexmethylphenidate hydrochloride
Inactive Ingredients:sugar spheres, methacrylic acid copolymers, triethyl citrate, talc, colloidal silicon dioxide, Hypromellose, polydextrose, triacetin, macrogol/PEG, FD&C Yellow #6/Sunset Yellow FCF AL, FD&C Blue #2/ indigo carmine AL, titanium dioxide and gelatin.

For Medication Guide, please visit www.parpharm.com
Manufactured by:
Par Pharmaceutical
Chestnut Ridge, NY 10977 U.S.A
Under License from:
Intellipharmaceutics Corp.
Toronto, Ontario M9W 5X2 CANADA

This Medication Guide has been approved by the U.S. Food and Drug Administration. Revised: 06/2020

PACKAGE LABEL.PRINCIPAL DISPLAY PANEL

PRINCIPAL DISPLAY PANEL - Dexmethyphnidate 15 mg Bottle Label
NDC 49884-428-01
Bottle of 100 capsules
Dexmethyphnidate HCL Extended-Release Capsules 15 mg

PRINCIPAL DISPLAY PANEL - Dexmethyphnidate 30 mg Bottle Label
NDC 49884-430-01
Bottle of 100 capsules
Dexmethyphnidate HCL Extended-Release Capsules 30 mg